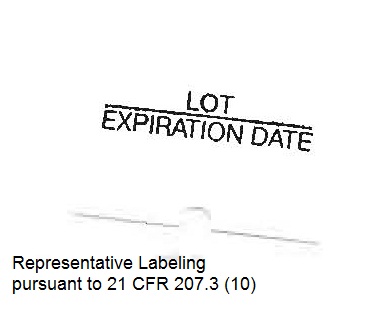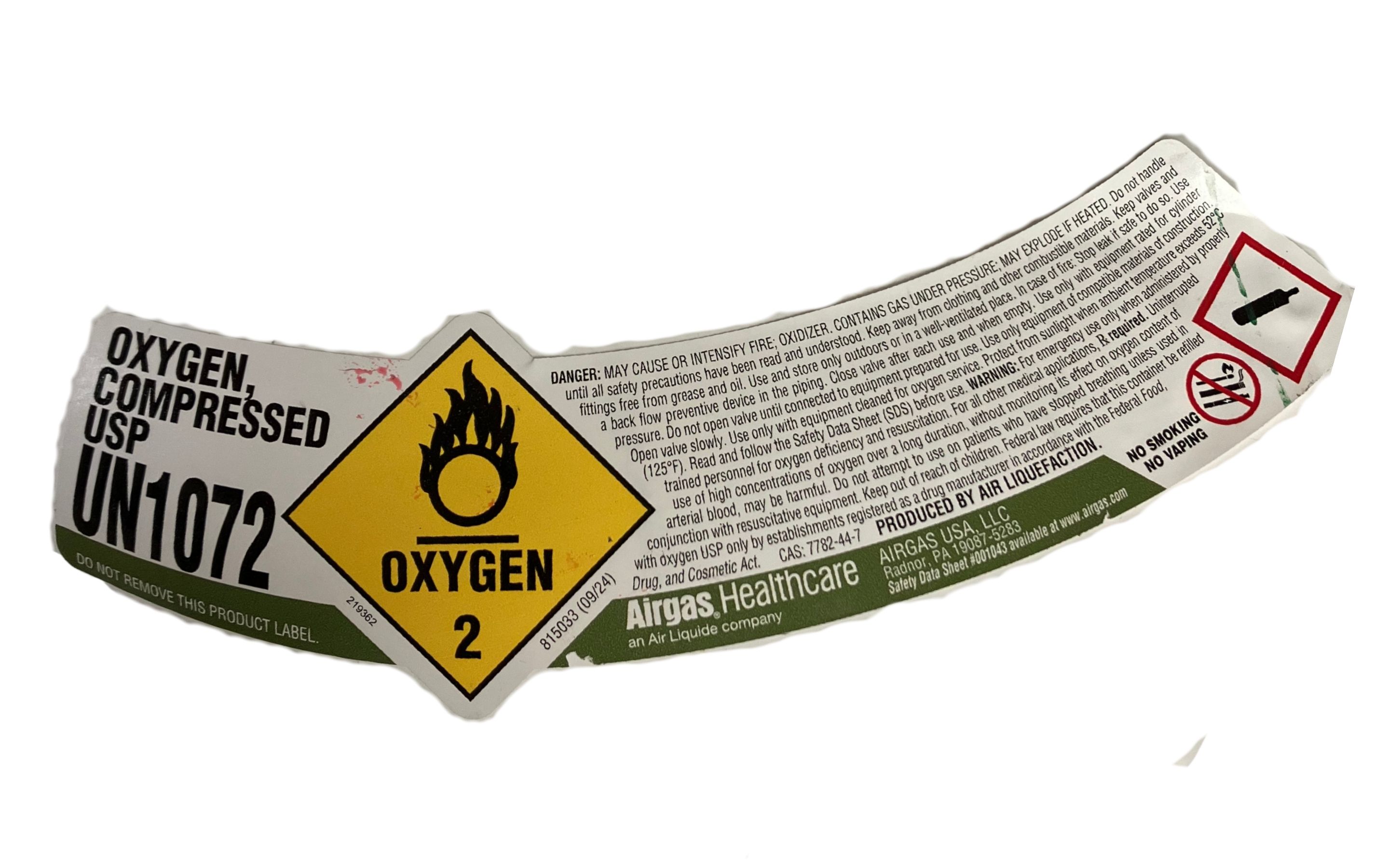 DRUG LABEL: Oxygen
NDC: 65208-123 | Form: GAS
Manufacturer: Loving Care and More Home Medical
Category: prescription | Type: HUMAN PRESCRIPTION DRUG LABEL
Date: 20251229

ACTIVE INGREDIENTS: OXYGEN 99 L/100 L

Oxygen

Prinicipal for Oxygen Product

OXYGEN, COMPRESSED USP

UN1072

DO NOT REMOVE THIS PRODUCT LABEL.

OXYGEN

2

DANGER: MAY CAUSE OR INTENSIFY FIRE; OXIDIZER. CONTAINS GAS UNDER PRESSURE; MAY EXPLODE IF HEATED.

Do not handle until all safety precautions have been read and understood. Keep away from combustible materials. Keep valves and fittings free from grease and oil. Use and store outdoors or in a well-ventilated place. If fire occurs: Stop leak if safe to do so. Use a back flow preventive device in the piping. Close valve after each use and when empty. Use equipment rated for cylinder pressure. Do not open valve until connected. Open valve slowly. Use only with equipment cleaned for oxygen service. Use only equipment of compatible materials of construction. Protect from sunlight when ambient temperature exceeds 52°C (125°F). Read and follow the Safety Data Sheet (SDS) before use. WARNING: For emergency use only. Use of high concentrations of oxygen over a long duration may be harmful. Federal law prohibits dispensing without prescription. For medical applications, oxygen USP must be used. Keep out of reach of children. Rx only.

CAS: 7782-44-7

PRODUCED BY AIR LIQUEFACTION

Airgas Healthcare

an Air Liquide company

AIRGAS USA, LLC

Radnor, PA 19087-5283

Safety Data Sheet: 800-403-7283

www.airgas.com

NO SMOKING

NO VAPING